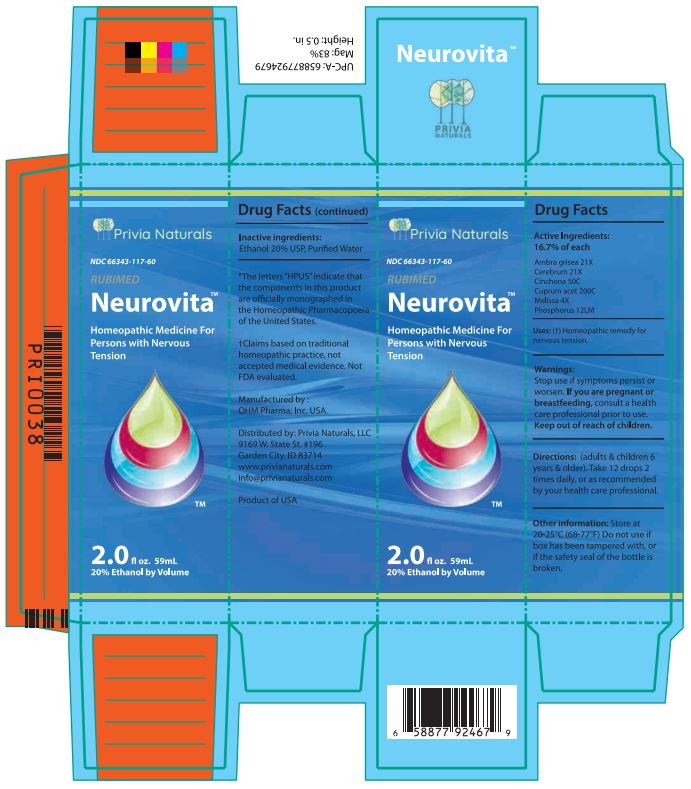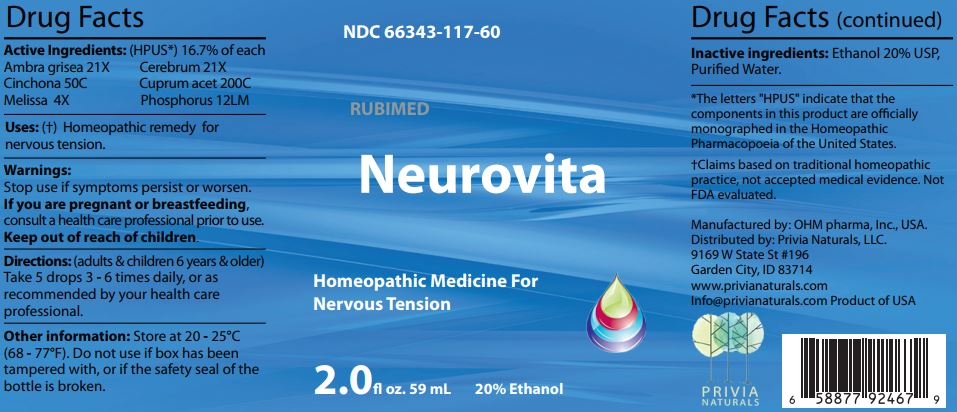 DRUG LABEL: Neurovita
NDC: 66343-117 | Form: LIQUID
Manufacturer: RUBIMED AG
Category: homeopathic | Type: HUMAN OTC DRUG LABEL
Date: 20260205

ACTIVE INGREDIENTS: AMBERGRIS 21 [hp_X]/60 mL; SUS SCROFA CEREBRUM 21 [hp_X]/60 mL; CINCHONA OFFICINALIS BARK 50 [hp_C]/60 mL; CUPRIC ACETATE 200 [hp_C]/60 mL; MELISSA OFFICINALIS WHOLE 4 [hp_X]/60 mL; PHOSPHORUS 12 [hp_M]/60 mL
INACTIVE INGREDIENTS: ALCOHOL; WATER

Neurovita

ACTIVE INGREDIENT

Drug Facts Active Ingredients: (HPUS*) 16.7% of each

Ambra grisea 21X Cerebrum 21X
Cinchona 50C Cuprum acet 200C
Melissa 4X Phosphorus 12LM

*The letters "HPUS" indicate that the components in this product are officially monographed in the Homeopathic Pharmacopoeia of the United States. †Claims based on traditional homeopathic practice, not accepted medical evidence. Not FDA evaluated.

INDICATIONS AND USAGE

Uses: (†) Homeopathic remedy for nervous tension.

Warnings:

Stop use if symptoms persist or worsen.

If you are pregnant or breastfeeding,consult a healthcare professional prior to use.

Keep out of reach of children.

DOSAGE AND ADMINISTRATION

Directions: (adults & children 6 years & older)

Take 5 drops 3-6 times daily, or as

recommended by your health care

professional.

Other information: Store at 20 - 25°C

(68 - 77°F.) Do not use if box has been

tampered with, or if the safety seal of the

bottle is broken.

Inactive ingredients:Ethanol 20% USP,

Purified Water.

QUESTIONS

Manufactured by: OHM pharma, Inc, USA.

Distributed by: Privia Naturals, LLC.

9169 W State St #196

Garden City, ID 83714

www.privianaturals.com

Info@privianaturals.com Product of USA.

PACKAGE LABEL

NDC 66343-117-60

RUBIMED

Neurovita

Homeopathic Medicine For

Nervous Tension

2.0 fl oz. 59mL 20% Ethanol

PURPOSE

Homeopathic Remedy For

Nervous Tension